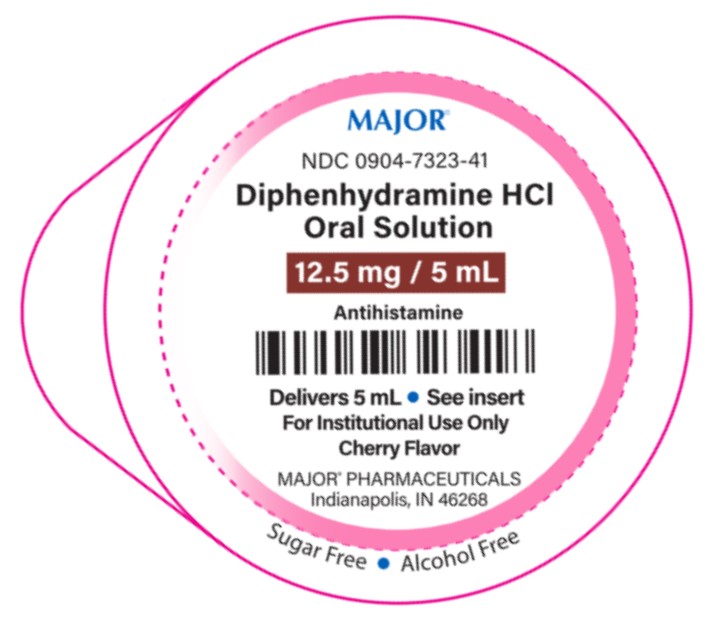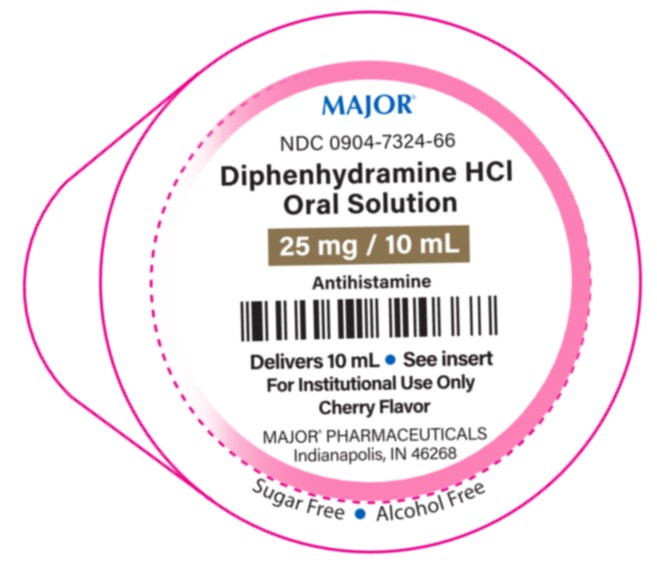 DRUG LABEL: Diphenhydramine HCl Oral Solution
NDC: 0904-7323 | Form: SOLUTION
Manufacturer: Major Pharmaceuticals
Category: otc | Type: HUMAN OTC DRUG LABEL
Date: 20250904

ACTIVE INGREDIENTS: DIPHENHYDRAMINE HYDROCHLORIDE 12.5 mg/5 mL
INACTIVE INGREDIENTS: CITRIC ACID MONOHYDRATE; FD&C RED NO. 40; METHYLPARABEN; PROPYLENE GLYCOL; PROPYLPARABEN; WATER; SODIUM CITRATE, UNSPECIFIED FORM; SUCRALOSE

Diphenhydramine HCl Oral Solution 12.5 mg/5 mL
Diphenhydramine HCl Oral Solution 25 mg/10 mL

Drug Facts

Active ingredient per 5 mL (1 Unit Dose)

Diphenhydramine HCl 12.5 mg

Active ingredient per 10 mL (1 Unit Dose)

Diphenhydramine HCl 25 mg

Purpose

Antihistamine

Uses

Temporarily relieves these symptoms due to hay fever or other respiratory allergies:

• runny nose • sneezing

• itchy, watery eyes • itching of the nose or throat

Warnings

Do not use

• to make a child sleepy
• with any other product containing diphenhydramine, even one used on skin

Ask a doctor before use if the child has

• a breathing problem such as chronic bronchitis
• glaucoma

Ask a doctor or pharmacist before use if the child istaking sedatives or tranquilizers

When using this product

• marked drowsiness may occur
• sedatives and tranquilizers may increase drowsiness
• excitability may occur, especially in children

Keep out of reach of children.In case of accidental overdose, get medical help or contact a Poison Control Center right away (1-800-222-1222)

Directions

For the 5 mL Unit-Dose:

• take every 4 to 6 hours, or as directed by a physician

• do not take more than 6 doses in 24 hours

age | dose
Children under 2 years of age | Do not use
Children 2 to under 6 years of age | Do not use unless directed by a doctor
Children 6 to under 12 years of age | 5 mL (12.5 mg) to 10 mL (25 mg)

Directions

For the 10 mL Unit-Dose:

• take every 4 to 6 hours, or as directed by a physician
• do not take more than 6 doses in 24 hours

age | dose
Children under 6 years of age | Do not use
Children 6 to under 12 years of age | 10 mL (25 mg)
Adults and children 12 years of age and over | 10 mL (25 mg) to 20 mL (50 mg)

Other information

• each 5 mL contains sodium: 3 mg
• store at 20° to 25°C (68° to 77°F). [See USP Controlled Room Temperature]
• do not use if lid is torn or broken

INACTIVE INGREDIENT

Inactive ingredients: citric acid, flavor, FD&C red#40, methylparaben, propylene glycol, propylparaben, purified water, sodium citrate, and sucralose

Questions or comments? (855) 879-4368

Distributed by:
MAJOR® PHARMACEUTICALS
Indianapolis, IN 46268

(800) 616-2471

PRINCIPAL DISPLAY PANEL

MAJOR®

NDC 0904-7323-41

Each 5 mL Contains:

Diphenhydramine HCL Oral Solution

12.5 mg/5 mL

Antihistamine

Delivers 5 mL • See insert

For Institutional Use Only

Cherry Flavor

MAJOR® PHARMACEUTICALS

Indianapolis, IN 46268

Sugar Free • Alcohol Free

PRINCIPAL DISPLAY PANEL

MAJOR®

NDC 0904-7324-66

Each 10 mL Contains:

Diphenhydramine HCL Oral Solution

25 mg/10 mL

Antihistamine

Delivers 10 mL • See insert

For Institutional Use Only

Cherry Flavor

MAJOR® PHARMACEUTICALS

Indianapolis, IN 46268

Sugar Free • Alcohol Free